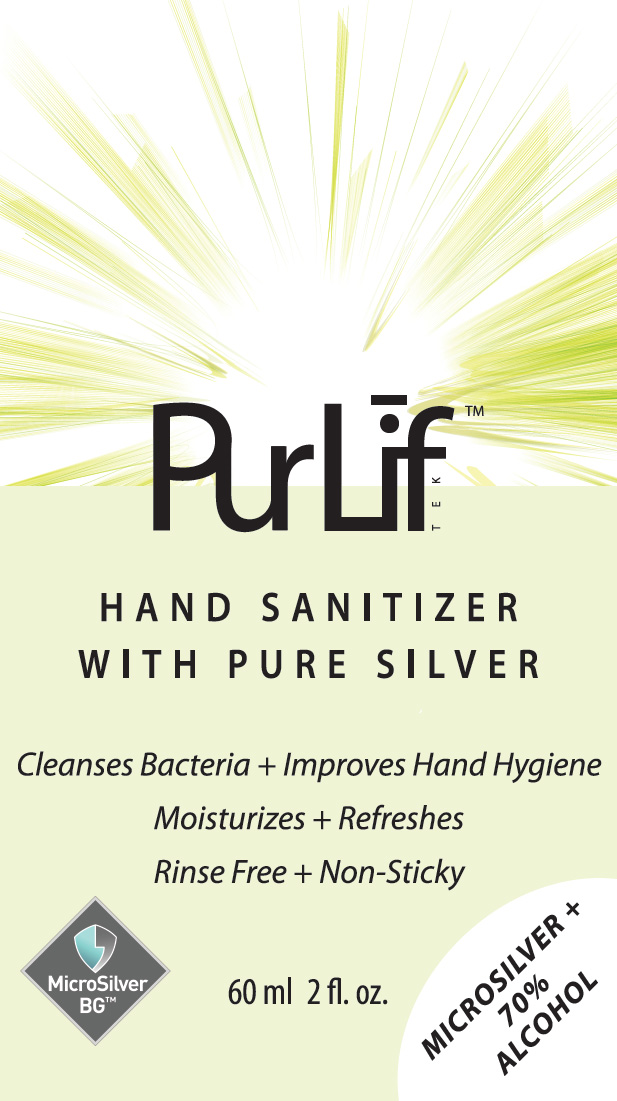 DRUG LABEL: PurLif Tek
NDC: 78994-002 | Form: GEL
Manufacturer: RFH BioTek Inc.
Category: otc | Type: HUMAN OTC DRUG LABEL
Date: 20220720

ACTIVE INGREDIENTS: ALCOHOL 70 mL/100 mL
INACTIVE INGREDIENTS: CARBOMER INTERPOLYMER TYPE A (ALLYL SUCROSE CROSSLINKED); GLYCERIN; CAPRYLYL GLYCOL; ETHYLHEXYLGLYCERIN; SILVER; WATER; AMINOMETHYLPROPANOL

PurLif Tek Hand sanitizer with Pure Silver

Active Ingredients

Alcohol 70% v/v

PURPOSE

Antiseptic

USE

This rinse-free hand gel sanitizer moisturizes the hand while cleaning and helps to reduce bacteria that potentially can cause disease.

WARNINGS

For External use only. Flammable. Keep away from heat or flame

DO NOT USE

On children less than 2 months of age. Avoid contact with broken skin

WHEN USING THIS PRODUCT

Keep out of eyes, ear and mouth. In case of contact with eyes, rinse eyes thoroughly with water.

STOP USE AND ASK A DOCTOR

If irritation or rash appears and lasts.

KEEP OUT OF REACH OF CHILDREN

If swallowed, get medical help and contact a Poison Control Centre right away.

DIRECTIONS

Put enough product in palm to cover hands. Rub briskly until dry. Supervise children under 6 years of age.

OTHER INFORMATION

Store in a cool, dry place, keep away from direct sunlight. Store between 15-30º C (59-86ºF). Avoid freezing and excess heat above 40ºC (104ºF).

INACTIVE INGREDIENTS

Water, Glycerin, Caprylyl Glycol, Ethylhexylglycerin, Acrylates/C10-30 Alkyl Acrylate Crosspolymer, Aminomethyl Propanol, Silver

PACKAGE LABEL

PurLif TEK

HAND SANITIZER

WITH PURE SILVER

Cleanses Bacteria + Improves Hand Hygiene

Moisturizes + Refreshes

Rinse Free + Non-Sticky

MicroSilver

BG™

MICROSOLVER +

70% ALCOHOL